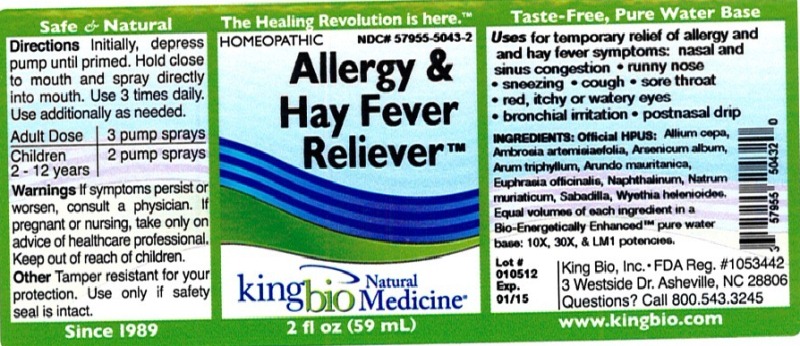 DRUG LABEL: Allergy and  Hay Fever Reliever
NDC: 57955-5043 | Form: LIQUID
Manufacturer: King Bio Inc
Category: homeopathic | Type: HUMAN OTC DRUG LABEL
Date: 20120619

ACTIVE INGREDIENTS: ONION 10 [hp_X]/59 mL; AMBROSIA ARTEMISIIFOLIA 10 [hp_X]/59 mL; ARSENIC TRIOXIDE 10 [hp_X]/59 mL; ARISAEMA TRIPHYLLUM ROOT 10 [hp_X]/59 mL; ARUNDO PLINIANA ROOT 10 [hp_X]/59 mL; EUPHRASIA STRICTA 10 [hp_X]/59 mL; NAPHTHALENE 10 [hp_X]/59 mL; SODIUM CHLORIDE 10 [hp_X]/59 mL; SCHOENOCAULON OFFICINALE SEED 10 [hp_X]/59 mL; WYETHIA HELENIOIDES ROOT 10 [hp_X]/59 mL
INACTIVE INGREDIENTS: WATER

Allergy and Hay Fever Reliever

Active Ingredients

Official HPUS: Allium cepa, Ambrosia artemisiaefolia, Arsenicum album, Arum triphyllum, Arundo mauritanica, Euphrasia officinalis, Naphthalinum, Natrum muriaticum, Sabadilla and Wyethia helenioides.

Reference image allergy and hay fever.jpg

Inactive Ingredient

Equal volumes of each ingredient in a Bio-Energetically Enhanced pure water base: 10X, 30X and LM1 potencies.

Reference image allergy and hay fever.jpg

Purpose

Uses for temporary relief of allergy and hay fever symptoms:

- nasal and sinus congestion
- runny nose
- sneezing
- cough
- sore throat
- red, itchy or watery eyes
- bronchial irritation
- postnasal drip

Reference image allergy and hay fever.jpg

Dosage and Administration

Directions: Initially, depress pump until primed. Hold close to mouth and spray directly into mouth. Use 3 times daily. Use additionally as needed.

Adult Dose 3 pump sprays

Children 2 - 12 years 2 pump sprays

Reference image allergy and hay fever.jpg

Warnings

If symptoms persist or worsen, consult a physician. If pregnant or nursing, take only on advice of healthcare professional. Keep out of reach of children.

Other: Tamper resistant for your protection. Use only if safety seal is intact.

Reference image allergy and hay fever.jpg

Keep out of reach of children.

Reference image allergy and hay fever.jpg

Indications and Usage

Uses for temporary relief of allergy and hay fever symptoms: nasal and sinus congestion, runny nose, sneezing, cough, sore throat, red, itchy or watery eyes, bronchial irritation, postnasal drip.
Reference image allergy and hay fever.jpg

PACKAGE LABEL

King Bio, Inc

3 Westside Dr.

Asheville, NC 28806

Questions? Call 800.543.3245

www.kingbio.com